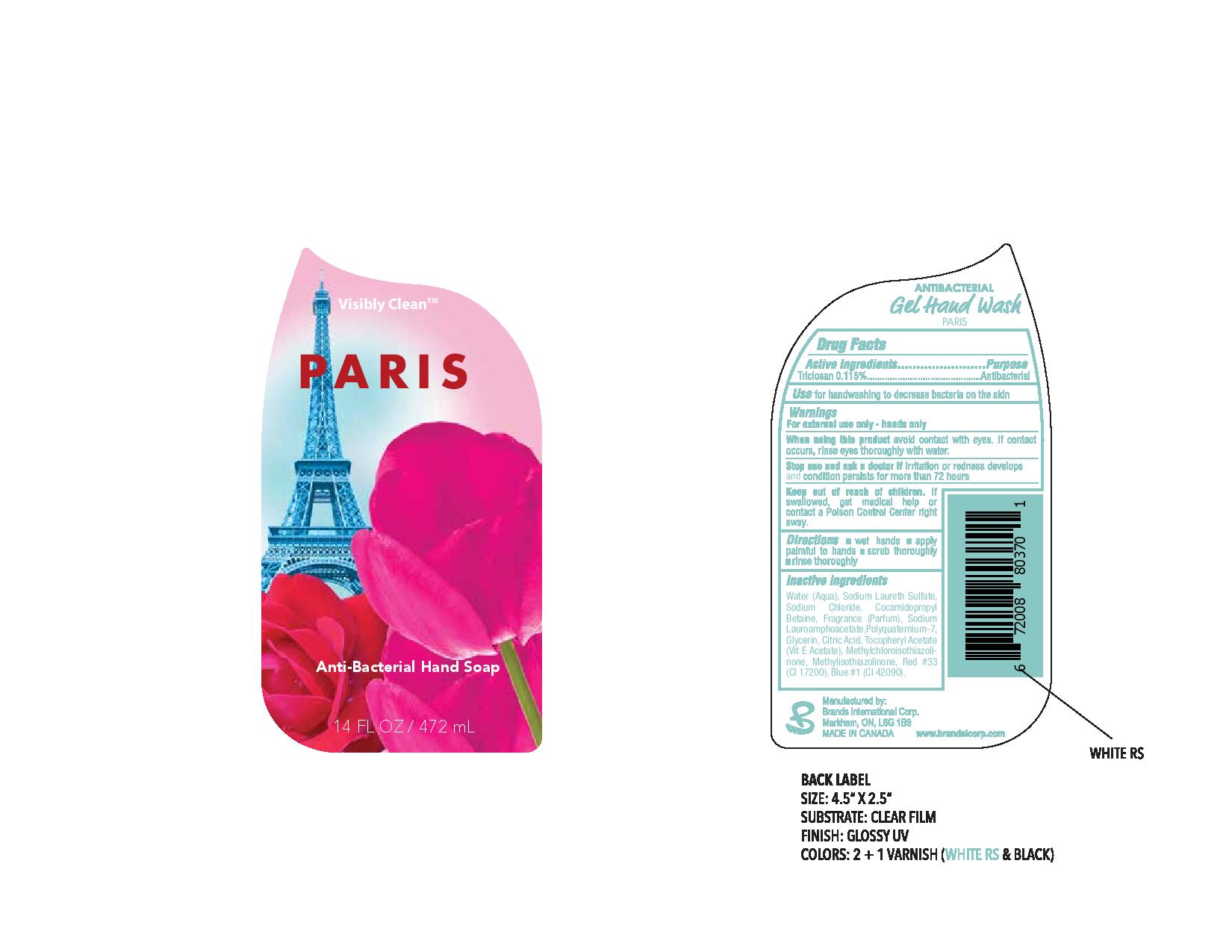 DRUG LABEL: Antibacterial
NDC: 50157-203 | Form: LIQUID
Manufacturer: Brands International Corp
Category: otc | Type: HUMAN OTC DRUG LABEL
Date: 20160506

ACTIVE INGREDIENTS: TRICLOSAN 1.15 mg/100 mL
INACTIVE INGREDIENTS: SODIUM LAUROAMPHOACETATE; POLYQUATERNIUM-7 (70/30 ACRYLAMIDE/DADMAC; 1600 KD); GLYCERIN; ANHYDROUS CITRIC ACID; .ALPHA.-TOCOPHEROL ACETATE; METHYLISOTHIAZOLINONE; METHYLCHLOROISOTHIAZOLINONE; D&C RED NO. 33; FD&C BLUE NO. 1; WATER; SODIUM LAURETH SULFATE; SODIUM CHLORIDE; COCAMIDOPROPYL BETAINE

Active Ingredient - Triclosan 0.115%

Purpose - Antibacterial

INDICATIONS AND USAGE

Use for handwashing to decrease bacteria on the skin

Warning

For external use only - hands only

When using this product avoid contact with eyes. If contact occurs, rinse eyes thoroughly with water

Stop use and ask a doctor if irritation or redness develops and condition persists for more than 72 hours

Keep out of reach of children. if swallowed, get medical help or contact a Poison Control Center right away

DOSAGE AND ADMINISTRATION

Direction

- wet hands
- apply palmful to hands
- scrub thoroughly
- rinse thoroughly

INACTIVE INGREDIENT

Water (Aqua), Sodium Laureth Sulfate, Sodium Chloride, Cocamidopropyl Betaine, Fragrance (Parfum), Sodium Lauroamphoacetate, Polyquaternium 7, Glycerin, Citric Acid, Tocopheryl Acetate (Vit E Actetate), Methylchloroisothiazolinone, Methylisothiazolinone, Red 33 (Cl 17200), Blue 1 (42090)